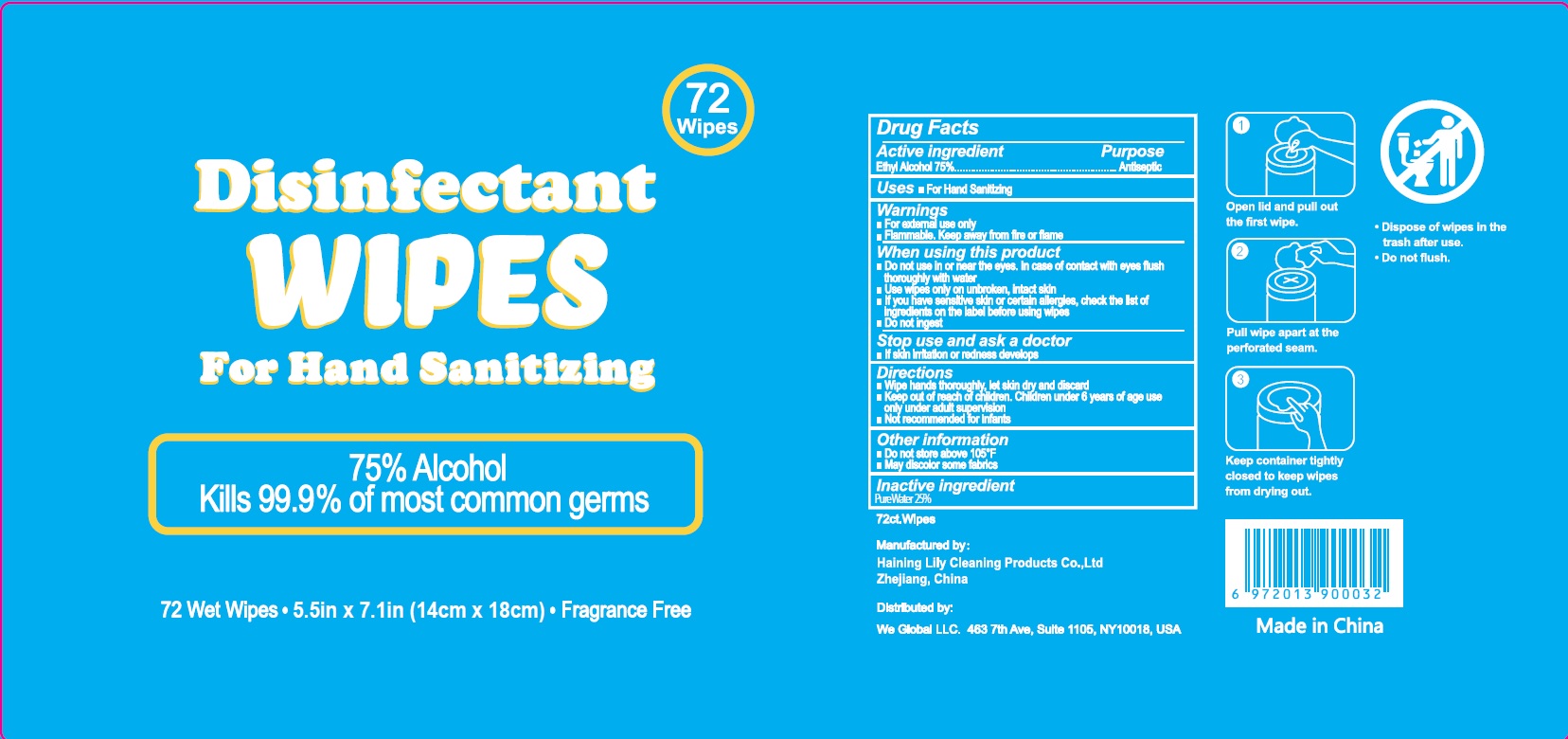 DRUG LABEL: Disinfectant Wipes for hand sanitizing
NDC: 77435-114 | Form: SWAB
Manufacturer: HAINING LILY CLEANING PRODUCTS CO., LTD
Category: otc | Type: HUMAN OTC DRUG LABEL
Date: 20200805

ACTIVE INGREDIENTS: ALCOHOL 75 g/100 g
INACTIVE INGREDIENTS: water

Wipes

Active Ingredient

Ethyl Alcohol 75%

Purpose

Antiseptic

USE

- For hand sanitizing

Warning

- Flammable, keep away from fire or flame.
- For external use only.

When using this product

- Do not use in or near the eyes. In case of contact, rinse eyes thoroughly with water.
- Use wipes only on unbroken, intact skin
- If you hve sensitive skin or certain allergies, check the east of ingredients on the label bofre using wipes.
- Do not ingest.

Stop use and ask a doctor

- if skin irritation or rednes develops.

Other Information：

- Do not store above 105℉
- May discolor some fabriks

KEEP OUT OF REACH OF CHILDREN

Children under 6 years of age use only under adult supvision.

Directions

- Wipe hands thoroughly, let skin dry and discard.
- Keep out of reach of children, children under 6 years of age use only under adult supervision
- Not recommended for infants

Inactive ingredients

Pure Water